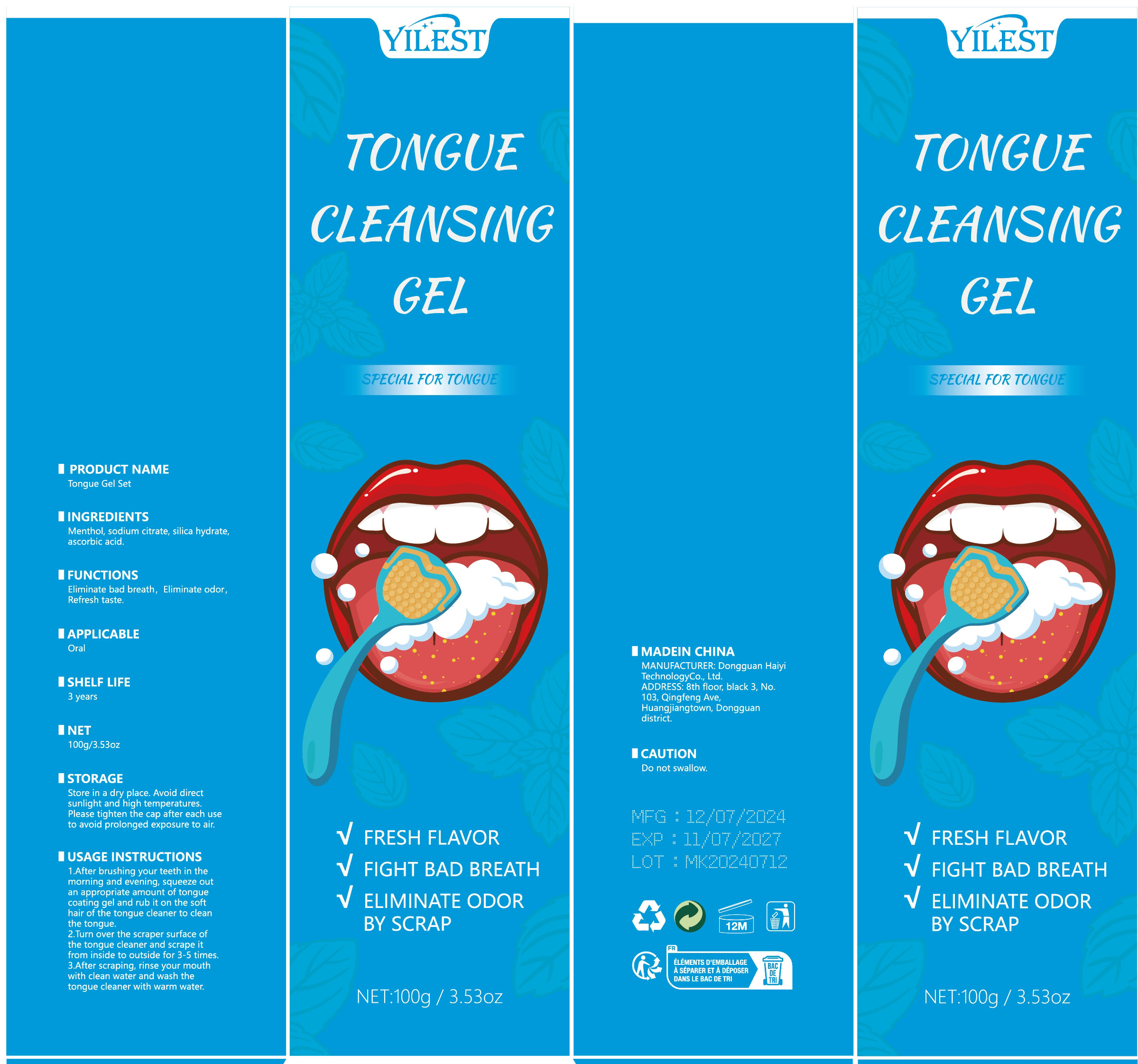 DRUG LABEL: Tongue Gel Set
NDC: 84732-060 | Form: PASTE
Manufacturer: Dongguan Haiyi Technology Co.,Ltd.
Category: otc | Type: HUMAN OTC DRUG LABEL
Date: 20241022

ACTIVE INGREDIENTS: MENTHOL 1 mg/100 g
INACTIVE INGREDIENTS: HYDRATED SILICA; ASCORBIC ACID; SODIUM CITRATE

Active ingredient

Menthol

Inactive ingredient

sodium citrate, silica hydrate,ascorbic acid.

Purpose section

Eliminate bad breath, Eliminate odor，Refresh taste.

Warning

Do not swallow.

stop use

This product may cause allergic reactions in asmall number of people.

not use

Not suitable for use by children, pregnantor breast feeding people.

OUT OF CHILDREN

KEEP THE PRODUCT OUT OF REACH OF CHILDREN to

HOW TO USE

1.After brushing your teeth in themorning and evening, squeeze outan appropriate amount of tonguecoating gel and rub it on the softhair of the tongue cleaner to cleanthe tongue.

2.Turn over the scraper surface ofthe tongue cleaner and scrape itfrom inside to outside for 3-5 times.

3.After scraping, rinse your mouthwith clean water and wash thetongue cleaner with warm water.

Dosage

Once a day in the morning and evening